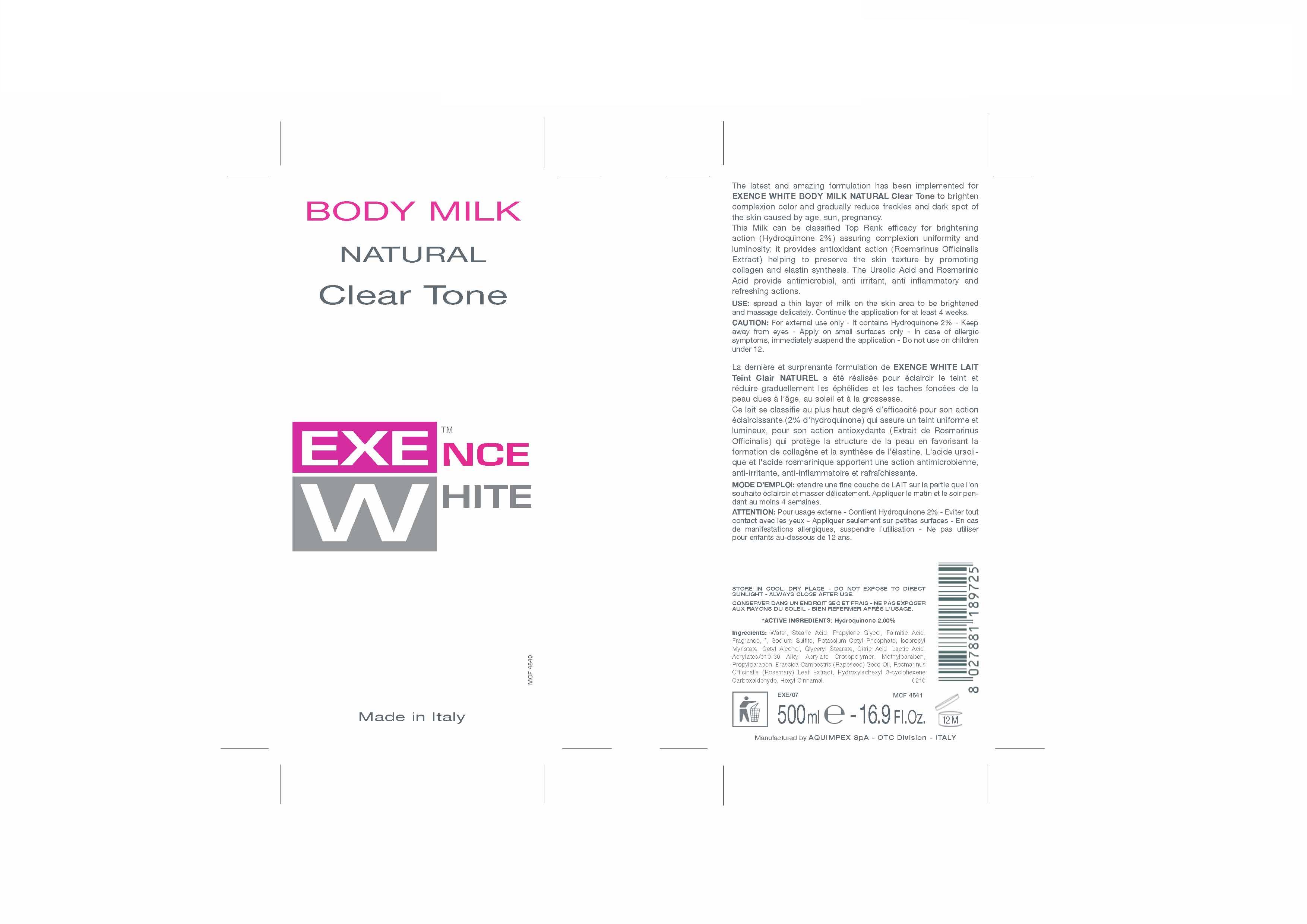 DRUG LABEL: EXENCE WHITE
NDC: 66273-0002 | Form: LOTION
Manufacturer: AQUIMPEX SPA
Category: otc | Type: HUMAN OTC DRUG LABEL
Date: 20110712

ACTIVE INGREDIENTS: HYDROQUINONE 4 mL/200 mL
INACTIVE INGREDIENTS: WATER; ROSEMARY; METHYLPARABEN; PROPYLENE GLYCOL; CARBOMER 934; CETYL ALCOHOL; STEARIC ACID; PALMITIC ACID; GLYCERYL MONOSTEARATE; ISOPROPYL MYRISTATE; POTASSIUM CETYL PHOSPHATE; PROPYLPARABEN; CITRIC ACID MONOHYDRATE; LACTIC ACID; SODIUM SULFITE; BRASSICA RAPA VAR. RAPA OIL

Exence White Body Milk Natural Clear Tone

Natural Clear Tone - Lightening

The latest and amazing formulation has been implemented for EXENCE WHITE BODY MILK NATURAL Clear Tone to brighten complexion color and gradually reduce freckles and dark spot of
the skin caused by age, sun, pregnancy.
This Milk can be classified Top Rank efficacy for brightening action (Hydroquinone 2%) assuring complexion uniformity and luminosity; it provides antioxidant action (Rosmarinus Officinalis
Extract) helping to preserve the skin texture by promoting collagen and elastin synthesis. The Ursolic Acid and Rosmarinic Acid provide antimicrobial, anti irritant, anti inflammatory and
refreshing actions.

Use

USE: spread a thin layer of milk on the skin area to be brightened and massage delicately. Continue the application for at least 4 weeks.

Caution

CAUTION: For external use only - It contains Hydroquinone 2% - Keep away from eyes - Apply on small surfaces only - In case of allergic symptoms, immediately suspend the application - Do not use on children under 12.

Active Ingredients

ACTIVE INGREDIENTS: Hydroquinone 2.00%

Ingredients

Ingredients: Water, Stearic Acid, Propylene Glycol, Palmitic Acid, Fragrance, *, Sodium Sulfite, Potassium Cetyl Phosphate, Isopropyl Myristate, Cetyl Alcohol, Glyceryl Stearate, Citric Acid, Lactic Acid, Acrylates/c10-30 Alkyl Acrylate Crosspolymer, Methylparaben, Propylparaben, Brassica Campestris (Rapeseed) Seed Oil, Rosmarinus
Officinalis (Rosemary) Leaf Extract, Hydroxyisohexyl 3-cyclohexene Carboxaldehyde, Hexyl Cinnamal.

STORAGE AND HANDLING

STORE IN COOL, DRY PLACE - DO NOT EXPOSE TO DIRECT SUNLIGHT - ALWAYS CLOSE AFTER USE.

Caution

CAUTION: For external use only - It contains Hydroquinone 2% - Keep away from eyes - Apply on small surfaces only - In case of allergic symptoms, immediately suspend the application - Do not use on children under 12.

Use

USE: spread a thin layer of milk on the skin area to be brightened and massage delicately. Continue the application for at least 4 weeks.